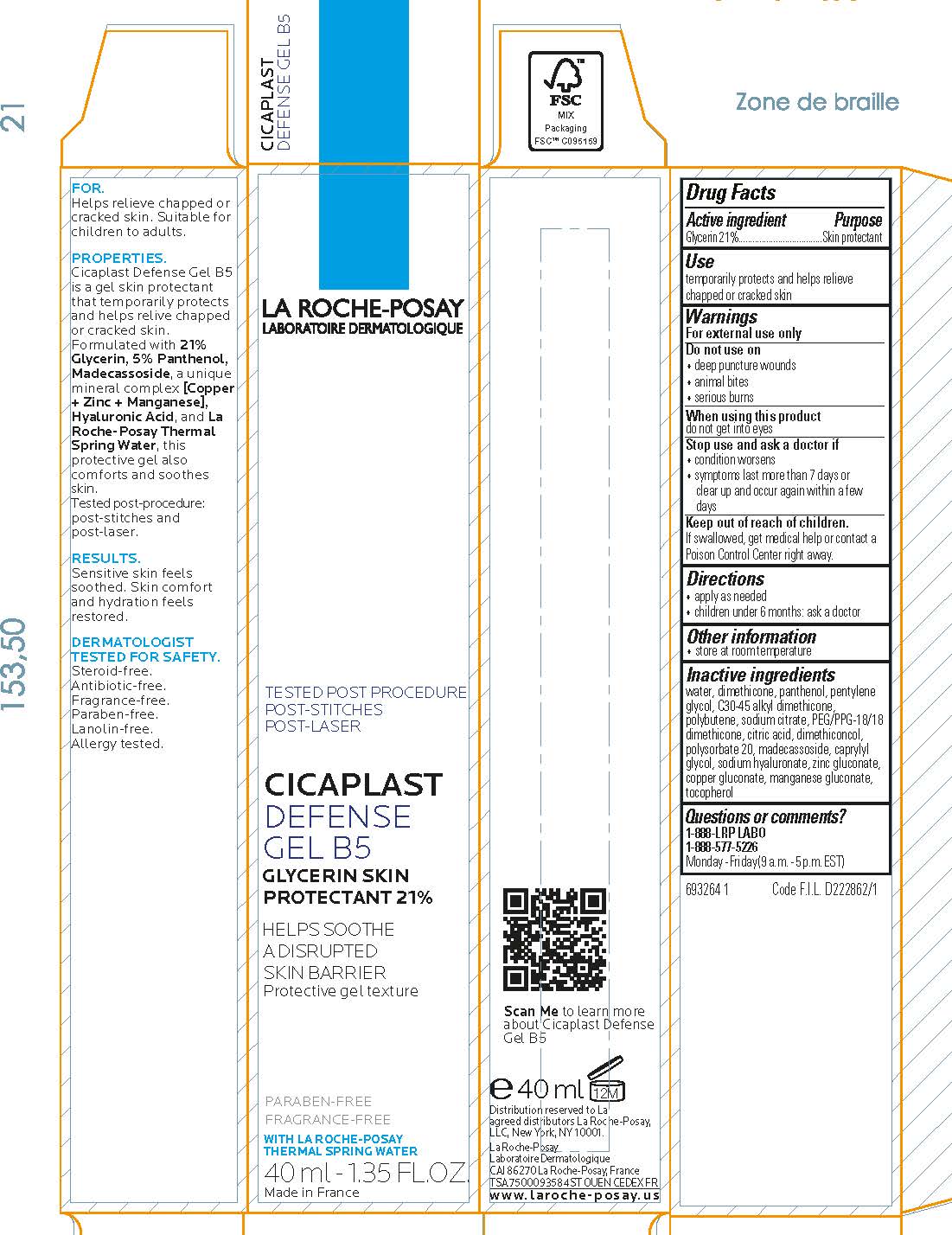 DRUG LABEL: La Roche Posay Laboratoire Dermatologique Cicaplast Defense B5
NDC: 69625-587 | Form: GEL
Manufacturer: Cosmetique Active Production
Category: otc | Type: HUMAN OTC DRUG LABEL
Date: 20231211

ACTIVE INGREDIENTS: GLYCERIN 10 mg/1 mL
INACTIVE INGREDIENTS: WATER; DIMETHICONE; PANTHENOL; PENTYLENE GLYCOL; C30-45 ALKYL METHICONE; POLYBUTENE (1400 MW); SODIUM CITRATE; PEG/PPG-18/18 DIMETHICONE; CITRIC ACID MONOHYDRATE; DIMETHICONOL (2000 CST); POLYSORBATE 20; MADECASSOSIDE; CAPRYLYL GLYCOL; HYALURONATE SODIUM; ZINC GLUCONATE; COPPER GLUCONATE; MANGANESE GLUCONATE; TOCOPHEROL

Drug Facts

Active ingredient

Glycerin 21%

Purpose

Skin protectant

Uses

- temporarily protects and helps relieve chapped or cracked skin

Warnings

For external use only

Do not use

- on deep or puncture wounds
- animal bites
- serious burns

When using this product

do not get into eyes

Stop use and ask a doctor if

- condition worsens
- symptoms last more than 7 days or clear up and occur again within a few days

Keep out of reach of children.

If swallowed, get medical help or contact a Poison Control Center right away.

Directions

- apply as needed

Other information

● store at room temperature

Inactive ingredients

water, dimethicone, panthenol, pentylene glycol, c30-45 alkyl dimethicone, polybutene, sodium citrate, PEG/PPG-18/18 dimethicone, citric acid, dimethiconol, polysorbate 20, madecassoside, caprylyl glycol, sodium hyaluronate, zinc gluconate, copper gluconate, manganese gluconate, tocopherol

Questions or comments?

1-888-LRP-LABO 1-888-577-5226

Monday - Friday (9 a.m. - 5 p.m. EST)